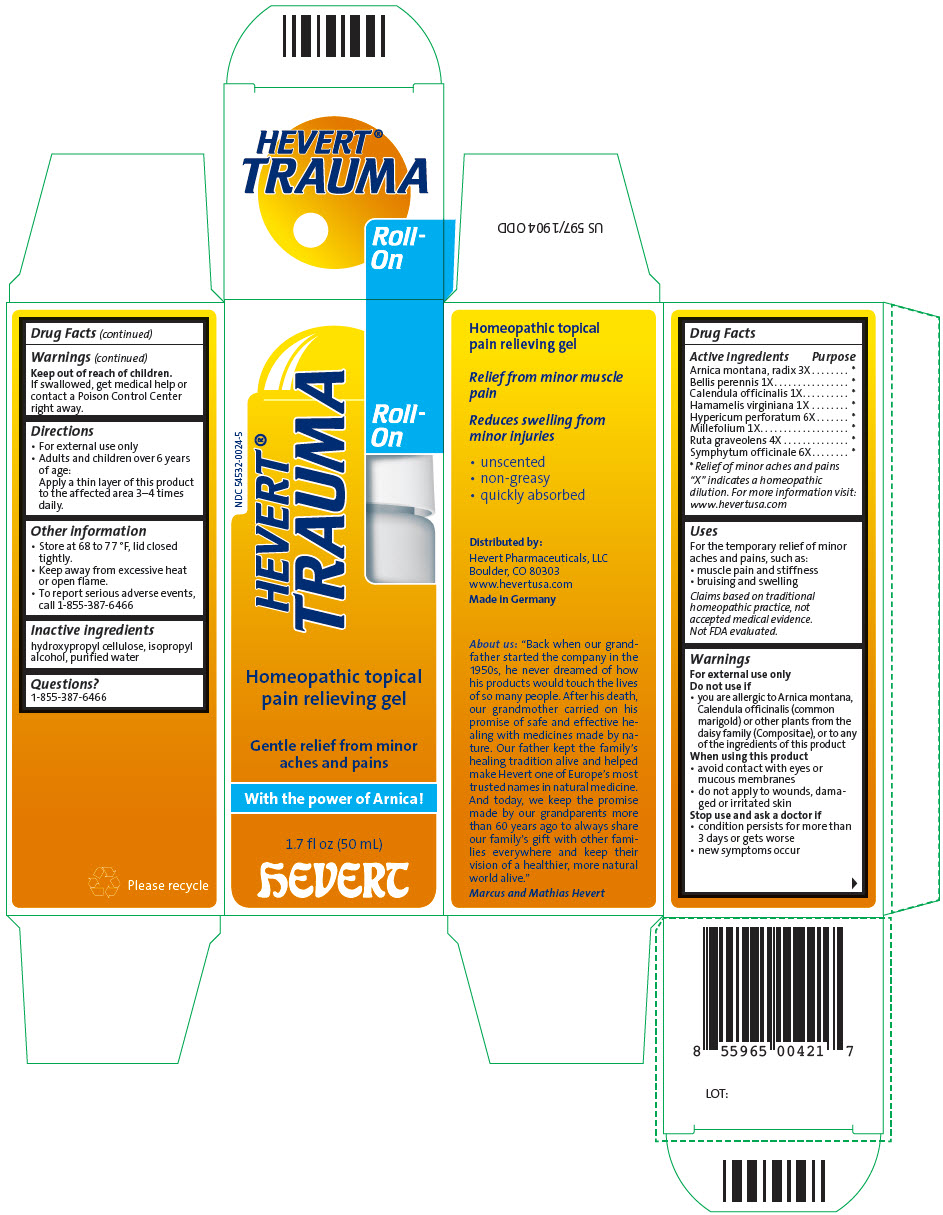 DRUG LABEL: Hevert Trauma Roll-On
NDC: 54532-0024 | Form: GEL
Manufacturer: Hevert Arzneimittel GmbH & Co KG
Category: homeopathic | Type: HUMAN OTC DRUG LABEL
Date: 20221215

ACTIVE INGREDIENTS: ARNICA MONTANA ROOT 3 [hp_X]/1 mL; BELLIS PERENNIS WHOLE 1 [hp_X]/1 mL; CALENDULA OFFICINALIS FLOWERING TOP 1 [hp_X]/1 mL; HAMAMELIS VIRGINIANA ROOT BARK/STEM BARK 1 [hp_X]/1 mL; HYPERICUM PERFORATUM WHOLE 6 [hp_X]/1 mL; ACHILLEA MILLEFOLIUM FLOWERING TOP 1 [hp_X]/1 mL; RUTA GRAVEOLENS FLOWERING TOP 4 [hp_X]/1 mL; COMFREY ROOT 6 [hp_X]/1 mL
INACTIVE INGREDIENTS: HYDROXYPROPYL CELLULOSE (1600000 WAMW); ISOPROPYL ALCOHOL; WATER

Hevert® Trauma Roll-On

Drug Facts

ACTIVE INGREDIENT

PURPOSE

Active ingredients

Purpose

Arnica montana, radix 3X

[Relief of minor aches and pains]

Bellis perennis 1X

Calendula officinalis 1X

Hamamelis virginiana 1X

Hypericum perforatum 6X

Millefolium 1X

Ruta graveolens 4X

Symphytum officinale 6X

"X" indicates a homeopathic dilution. For more information visit: www.hevertusa.com

Uses

For the temporary relief of minor aches and pains, such as:

- muscle pain and stiffness
- bruising and swelling

Claims based on traditional homeopathic practice, not accepted medical evidence. Not FDA evaluated.

Warnings

For external use only

Do not use if

- you are allergic to Arnica montana, Calendula officinalis (common marigold) or other plants from the daisy family (Compositae), or to any of the ingredients of this product

When using this product

- avoid contact with eyes or mucous membranes
- do not apply to wounds, damaged or irritated skin

Stop use and ask a doctor if

- condition persists for more than 3 days or gets worse
- new symptoms occur

Keep out of reach of children.

If swallowed, get medical help or contact a Poison Control Center right away.

Directions

- For external use only
- Adults and children over 6 years of age:
  Apply a thin layer of this product to the affected area 3–4 times daily.

Other information

- Store at 68 to 77 °F, lid closed tightly.
- Keep away from excessive heat or open flame.
- To report serious adverse events, call 1-855-387-6466

Inactive ingredients

hydroxypropyl cellulose, isopropyl alcohol, purified water

Questions?

1-855-387-6466

Distributed by:
Hevert Pharmaceuticals, LLC
Boulder, CO 80303

PRINCIPAL DISPLAY PANEL - 50 mL Bottle Carton

NDC 54532-0024-5

HEVERT®
TRAUMA

Roll-
On

Homeopathic topical
pain relieving gel

Gentle relief from minor
aches and pains

With the power of Arnica !

1.7 fl oz (50 mL)

hEVERT